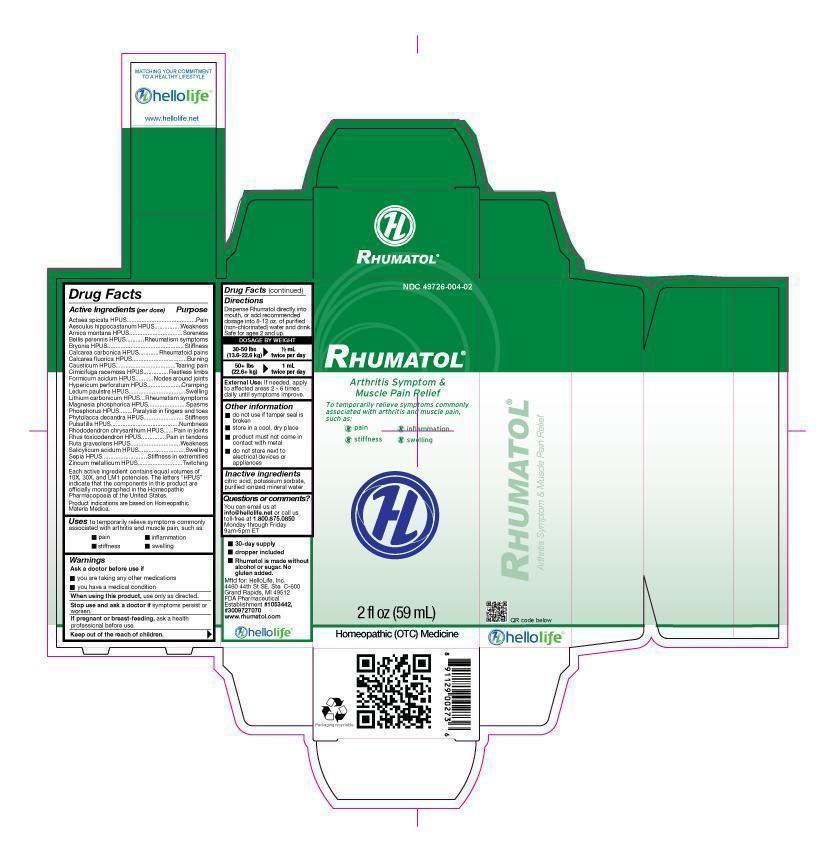 DRUG LABEL: Rhumatol
NDC: 49726-004 | Form: LIQUID
Manufacturer: Hello Life, Inc.
Category: homeopathic | Type: HUMAN OTC DRUG LABEL
Date: 20181226

ACTIVE INGREDIENTS: ACTAEA SPICATA ROOT 10 [hp_X]/59 mL; ARNICA MONTANA 10 [hp_X]/59 mL; BELLIS PERENNIS 10 [hp_X]/59 mL; BRYONIA ALBA ROOT 10 [hp_X]/59 mL; OYSTER SHELL CALCIUM CARBONATE, CRUDE 10 [hp_X]/59 mL; CALCIUM FLUORIDE 10 [hp_X]/59 mL; CAUSTICUM 10 [hp_X]/59 mL; BLACK COHOSH 10 [hp_X]/59 mL; FORMIC ACID 10 [hp_X]/59 mL; HYPERICUM PERFORATUM 10 [hp_X]/59 mL; LEDUM PALUSTRE TWIG 10 [hp_X]/59 mL; MAGNESIUM PHOSPHATE, TRIBASIC, PENTAHYDRATE 10 [hp_X]/59 mL; PHYTOLACCA AMERICANA ROOT 10 [hp_X]/59 mL; PULSATILLA VULGARIS 10 [hp_X]/59 mL; RHODODENDRON AUREUM LEAF 10 [hp_X]/59 mL; TOXICODENDRON PUBESCENS LEAF 10 [hp_X]/59 mL; RUTA GRAVEOLENS FLOWERING TOP 10 [hp_X]/59 mL; SALICYLIC ACID 10 [hp_X]/59 mL; HORSE CHESTNUT 10 [hp_X]/59 mL; PHOSPHORUS 10 [hp_X]/59 mL; LITHIUM CARBONATE 10 [hp_X]/59 mL; SEPIA OFFICINALIS JUICE 10 [hp_X]/59 mL; ZINC 10 [hp_X]/59 mL
INACTIVE INGREDIENTS: WATER; POTASSIUM SORBATE; CITRIC ACID MONOHYDRATE

Drug Facts

Active Ingredients (per dose)

Actaea spicata HPUS
Aesculus hippocastanum HPUS
Arnica montana HPUS
Bellis perennis HPUS
Bryonia HPUS
Calcarea carbonica HPUS
Calcarea fluorica HPUS
Causticum HPUS
Cimicifuga racemosa HPUS
Formicum acidum HPUS
Hypericum perforatum HPUS
Ledum paulstre HPUS
Lithium carbonicum HPUS
Magnesia phosphorica HPUS
Phosphorus HPUS
Phytolacca decandra HPUS
Pulsatilla HPUS
Rhododendron chrysanthum HPUS
Rhus toxicodendron HPUS
Ruta graveolens HPUS
Salicylicum acidum HPUS
Sepia HPUS
Zincum metallicum HPUS

Each ingredient contains equal volumes of 10X, 30X and LM1 potencies. The letters “HPUS” indicate that the components in this product are officially monographed in the Homeopathic Pharmacopoeia of the United States.
Product indications are based on Homeopathic Materia Medica. Product indicatiosn are based on Homeopathic Materia Medica.

Purpose

Actaea spicata HPUS.........................................Pain
Aesculus hippocastanum HPUS.................Weakness
Arnica montana HPUS................................Soreness
Bellis perennis HPUS............Rheumatism symptoms
Bryonia HPUS.............................................Stiffness
Calcarea carbonica HPUS.............Rheumatoid pains
Calcarea fluorica HPUS................................Burning
Causticum HPUS...................................Tearing pain
Cimicifuga racemosa HPUS…...............Restless limbs
Formicum acidum HPUS...........Nodes around joints
Hypericum perforatum HPUS....................Cramping
Ledum paulstre HPUS..................................Swelling
Lithium carbonicum HPUS....Rheumatism symptoms
Magnesia phosphorica HPUS........................Spasms
Phosphorus HPUS..........Paralysis in fingers and toes
Phytolacca decandra HPUS.........................Stiffness
Pulsatilla HPUS........................................Numbness
Rhododendron chrysanthum HPUS......Pain in joints
Rhus toxicodendron HPUS...............Pain in tendons
Ruta graveolens HPUS.............................Weakness
Salicylicum acidum HPUS............................Swelling
Sepia HPUS...........................Stiffness in extremities
Zincum metallicum HPUS..........................Twitching

Uses

to temporarily relieve symptoms commonly associated with arthritis and muscle pain, such as:
• pain
• inflammation
• stiffness
• swelling

Warnings

Ask a doctor before use if

• you are taking any other medications
• you have a medical condition

When using this product,

use only as directed.

Stop use and ask a doctor if

symptoms persist or worsen.

If pregnant or breast-feeding,

ask a health professional before use.

Keep out of the reach of children.

Directions

Dispense Rhumatol directly into mouth, or add recommended dosage into 8-12 oz. of purified (non-chlorinated) water and drink. Safe for ages 2 and up.

DOSAGE BY WEIGHT

30-50 lbs 1/2 mL
(13.6-22.6 kg) twice per day
50+ lbs 1 mL
(22.6+ kg) twice per day

External Use: If needed, apply to affected areas 2 - 6 times daily until symptoms improve.

Other information

• do not use if tamper seal is broken
• store in a cool, dry place
• product must not come in contact with metal
• do not store next to electrical devices or appliances

Inactive ingredients

citric acid, potassium sorbate, purified ionized mineral water.

Questions or comments?

You can email us at info@hellolife.net or call us toll-free at
1.800.875.0850 Monday through Friday, 9am-5pm ET

DESCRIPTION

- 30-day supply
- dropper included
- Rhumatol is made without alcohol or sugar. No gluten added.

Mftd for: HelloLife, Inc.
4460 44th St. SE, Ste C-600
Grand Rapids, MI 49512
FDA Pharmaceutical Establishment
#1053442, #3009727070
www.rhumatol.com

Principal Display Panel

NDC 49726-004-02

Rhumatol®

Arthritis Symptom and Muscle Pain Relief
To temporarily relieve symptoms commonly associated with arthritis and muscle pain, such as:
• pain
• inflammation
• stiffness
• swelling
2 fl oz (59 mL)
Homeopathic (OTC) Medicine